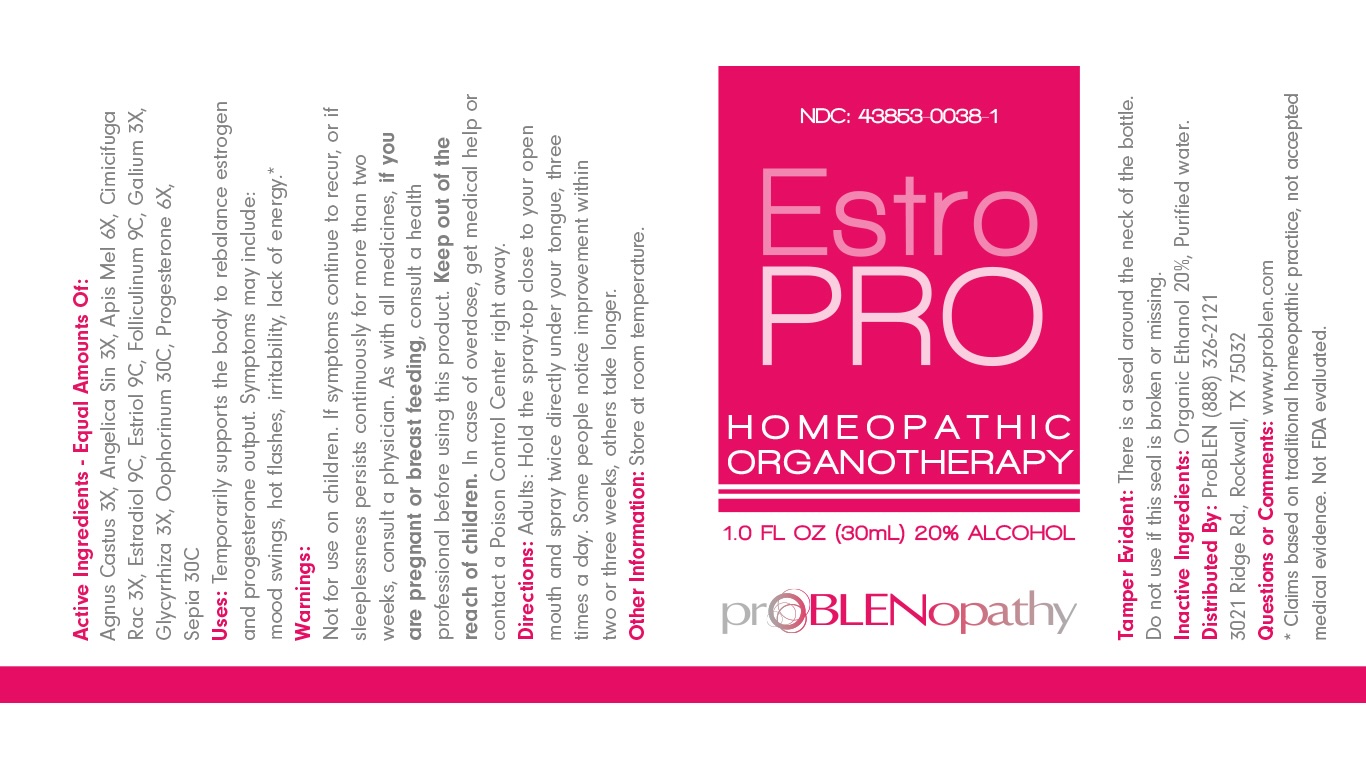 DRUG LABEL: EstroPRO
NDC: 43853-0038 | Form: SPRAY
Manufacturer: ProBlen
Category: homeopathic | Type: HUMAN OTC DRUG LABEL
Date: 20251222

ACTIVE INGREDIENTS: CHASTE TREE 3 [hp_X]/1 mL; ANGELICA SINENSIS ROOT 3 [hp_X]/1 mL; APIS MELLIFERA 6 [hp_X]/1 mL; BLACK COHOSH 3 [hp_X]/1 mL; ESTRADIOL 9 [hp_C]/1 mL; ESTRIOL 9 [hp_C]/1 mL; ESTRONE 9 [hp_C]/1 mL; GALIUM APARINE 3 [hp_X]/1 mL; GLYCYRRHIZA GLABRA 3 [hp_X]/1 mL; SUS SCROFA OVARY 30 [hp_C]/1 mL; PROGESTERONE 6 [hp_X]/1 mL; SEPIA OFFICINALIS JUICE 30 [hp_C]/1 mL
INACTIVE INGREDIENTS: WATER; ALCOHOL

EstroPRO Homeopathic Organotherapy

ACTIVE INGREDIENTS- Equal Amounts Of:

Agnus Castus 3X

Angelica Sin 3X

Apis Mel 6X

Cimicifuga Rac 3X

Estradiol 9C

Estriol 9C

Folliculinum 9C

Galium 3X

Glycyrrhiza 3X

Oophorinum 30C

Progesterone 6X

Sepia 30C

Active ingredients | Purpose
Agnus Castus, Angelica Sin, Apis Mel, Cimicifuga Rac, Estradiol, Estriol, Folliculinum, Galium, Glycyrrhiza, Oophorinum, Progesterone, Sepia | To rebalance estrogen and progesterone output

INDICATIONS AND USAGE

Uses: Temporarily supports the body to rebalance estrogen and progesterone output. Symptoms may include: mood swings, hot flashes, irritability, lack of energy.*

*Claims based on traditional homeopathic practice, not accepted medical evidence. Not FDA evaluated.

Warnings:

Not for use on children. If symptoms continue to recur, or if sleeplessness persists continuously for more than two weeks, consult a physician.

Keep out of reach of children. In case of overdose, get medical help or contact a Poison Control Center right away.

Pregnant or breast feeding

As with all medicines, if you are pregnant or breast feeding, consult a health professional before using this product.

DOSAGE AND ADMINISTRATION

Directions: Adults: Hold the spray-top close to your open mouth and spray twice directly under your tongue, three times a day. Some people notice improvement within two or three weeks, others take longer.

Inactive Ingredients: Organic Ethanol 20%, Purified water.

Distributed By: ProBLEN (888) 326-2121

3021 Ridge Rd., Rockwall, TX 75032

Other Information: Store at room temperature.

Tamper Evident: There is a seal around the neck of the bottle. Do not use if this seal is broken or missing.

Questions or Comments: www.problen.com